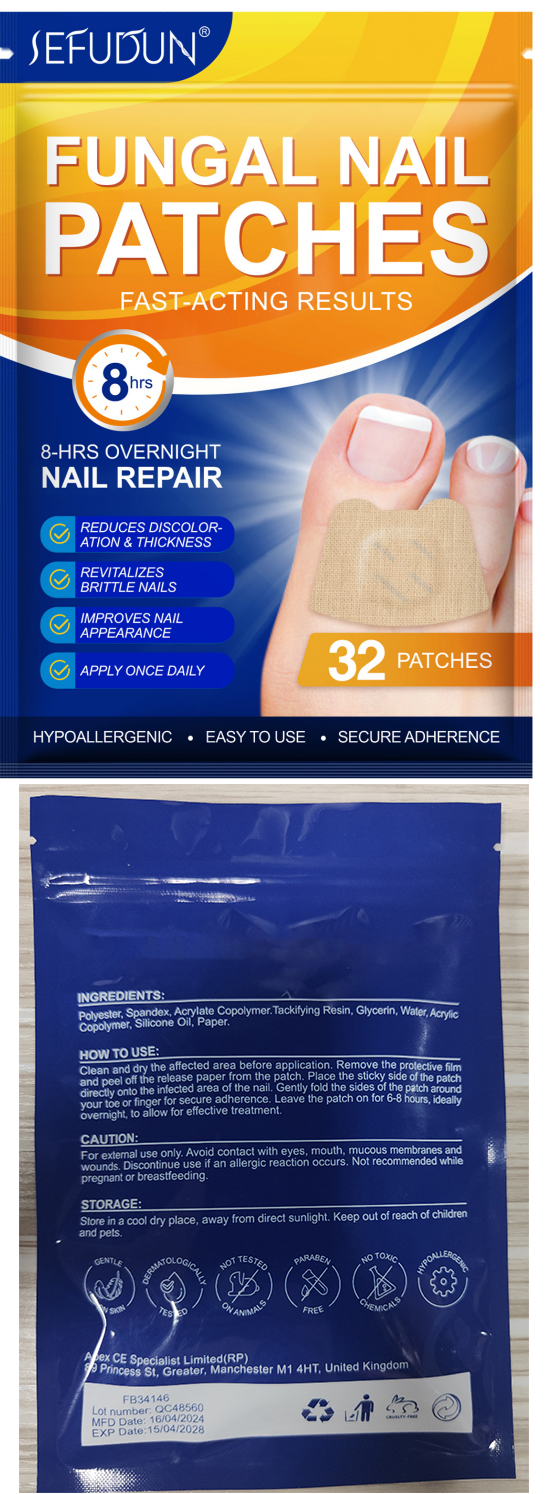 DRUG LABEL: SEFUDUN FUNGAL NAIL PATCHES
NDC: 83804-006 | Form: PATCH
Manufacturer: Shenzhen Shandian Jingling Technology Co., Ltd.
Category: otc | Type: HUMAN OTC DRUG LABEL
Date: 20250701

ACTIVE INGREDIENTS: GLYCERIN 0.01 g/1 1
INACTIVE INGREDIENTS: DIMETHICONE, UNSPECIFIED; POLYESTER (ADIPIC ACID, 1,6-HEXANEDIOL, NEOPENTYL GLYCOL)

83804-006 SEFUDUN FUNGAL NAIL PATCHES

ACTIVE INGREDIENT

Glycerin 1%

PURPOSE

antifungal

INDICATIONS AND USAGE

REDUCES DISCOLOR-ATION & THICKNESS, REVITALIZESBRITTLE NAILS，IMPROVES NAILAPPEARANCE

WARNINGS

For extemal use only.

Not recommended whilepregnant or breastfeeding.

WHEN USING

Avoid contact with eyes, mouth, mucous membranes and wounds.

Discontinue use if an allergic reaction occurs.

KEEP OUT OF REACH OF CHILDREN SECTION

DOSAGE AND ADMINISTRATION

Clean and dry the affecled area before application. Remove the prolective filmand peel off the release paper from the patch. Place the sticky side of the patchdirectiy onto the infected area of the nail. Gently fold the sides of the paich arotndyour toe or finger for secure adherence. Leave the patch on for 6.8 hours, ideallyovernight, to allow for effective treatment.

INACTIVE INGREDIENT

Polyester, Silicone Oil